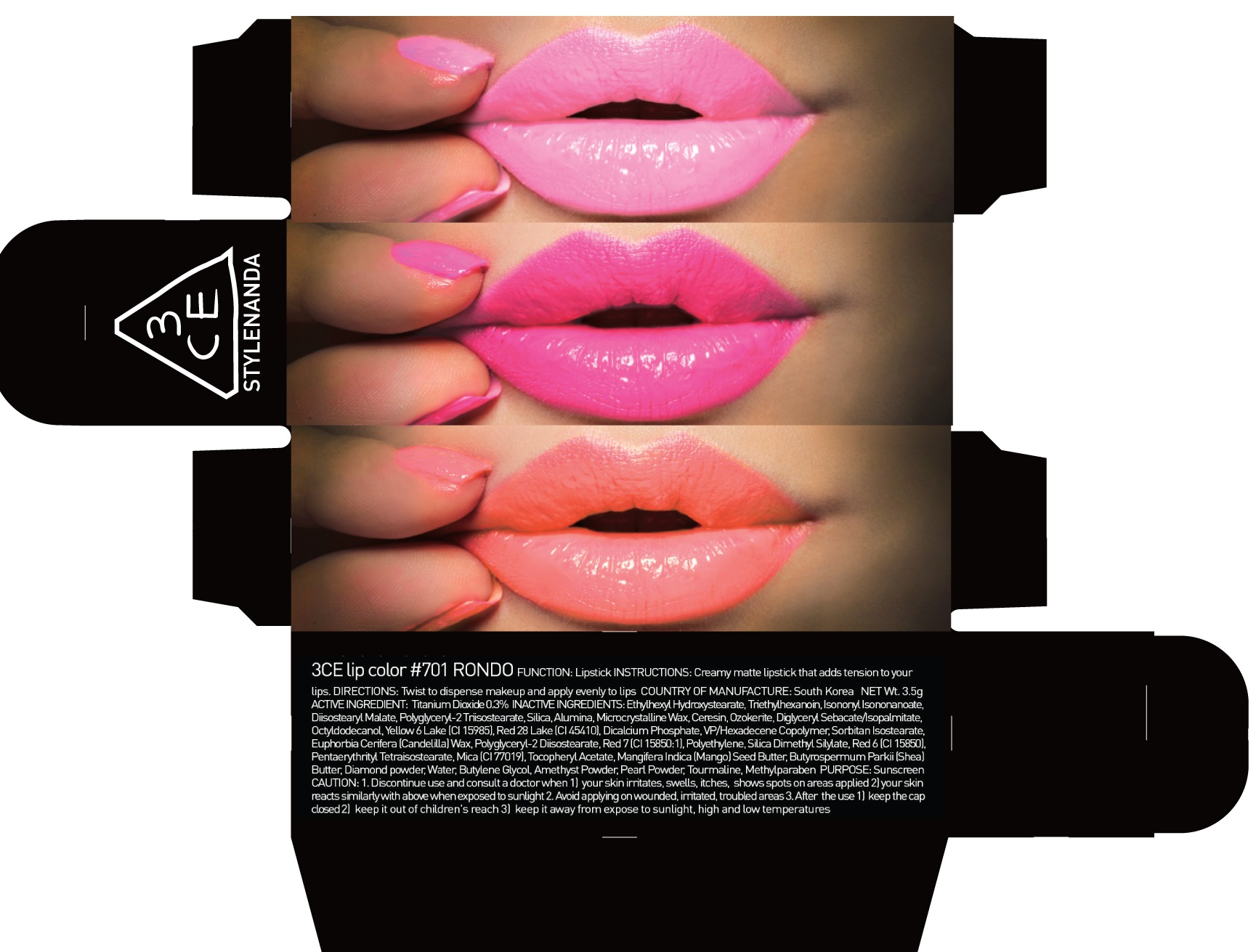 DRUG LABEL: 3CE LIP COLOR 701 RONDO
NDC: 60764-081 | Form: LIPSTICK
Manufacturer: Nanda Co., Ltd
Category: otc | Type: HUMAN OTC DRUG LABEL
Date: 20161007

ACTIVE INGREDIENTS: Titanium Dioxide 0.01 g/3.5 g
INACTIVE INGREDIENTS: Triethylhexanoin; Diisostearyl Malate

ACTIVE INGREDIENT

Active Ingredient: Titanium Dioxide 0.3%

INACTIVE INGREDIENT

Inactive Ingredients: EthylhexylHydroxystearate, Triethylhexanoin, IsononylIsononanoate, Diisostearyl Malate, Polyglyceryl-2 Triisostearate, Silica, Alumina, Microcrystalline Wax, Ceresin, Ozokerite, DiglycerylSebacate/Isopalmitate, Octyldodecanol, Yellow 6 Lake (CI 15985), Red 28 Lake (CI 45410), Dicalcium Phosphate, VP/Hexadecene Copolymer, SorbitanIsostearate, Euphorbia Cerifera (Candelilla) Wax, Polyglyceryl-2 Diisostearate, Red 7 (CI 15850:1), Polyethylene, Silica Dimethyl Silylate, Red 6 (CI 15850), PentaerythritylTetraisostearate, Mica (CI 77019), Tocopheryl Acetate, MangiferaIndica (Mango) Seed Butter, ButyrospermumParkii (Shea) Butter, Diamond powder, Water, Butylene Glycol, Amethyst Powder, Pearl Powder, Tourmaline, Methylparaben

PURPOSE

Purpose: Sunscreen

CAUTION

CAUTION: 1. Discontinue use and consult a doctor when - your skin irritates, swells, itches, shows spots on areas applied - your skin reacts similarly with above when exposed to sunlight 2. Avoid applying on wounded, irritated, troubled areas 3. After the use - keep the cap closed - keep it out of children's reach - keep it away from expose to sunlight, high and low temperatures

DESCRIPTION

INSTRUCTIONS: A rich color lipstick that moistly adheres to lips.

Directions: Twist to dispense makeup and apply evenly to lips